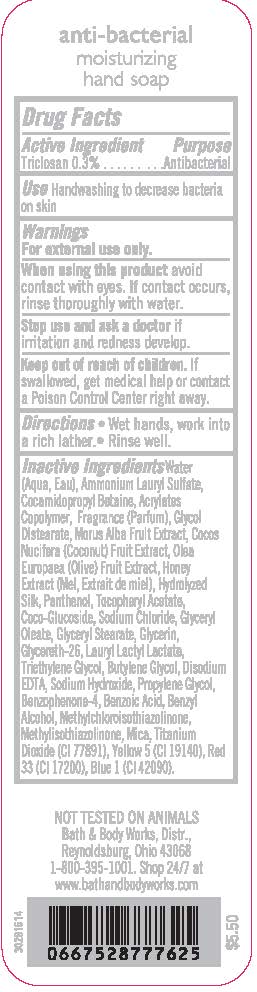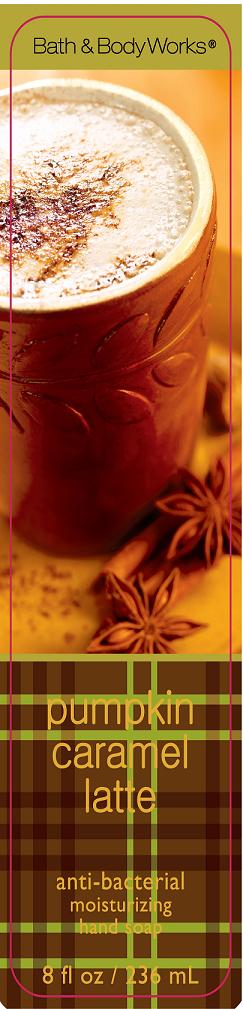 DRUG LABEL: Anti-Bacterial Moisturizing Hand
NDC: 62670-4164 | Form: SOAP
Manufacturer: Bath & Body Works, Inc.
Category: otc | Type: HUMAN OTC DRUG LABEL
Date: 20120403

ACTIVE INGREDIENTS: TRICLOSAN 3 mg/1 g
INACTIVE INGREDIENTS: WATER

DRUG FACTS

ACTIVE INGREDIENT

Triclosan 0.3%

PURPOSE

Antibacterial

USE

Handwashing to decrease bacteria on skin

WARNINGS

For external use only.

WHEN USING THIS PRODUCT

avoid contact with eyes. If contact occurs, rinse thoroughly with water.

STOP USE AND ASK A DOCTOR

if irritation and redness develop.

KEEP OUT OF REACH OF CHILDREN

If swallowed, get medical help or contact a Poison Control Center right away.

DIRECTIONS

- Wet hands, work into a rich lather.
- Rinse well.

INACTIVE INGREDIENTS

Water (Aqua, Eau), Ammonium Lauryl Sulfate, Cocamidopropyl Betaine, Acrylates Copolymer, Fragrance (Parfum), Glycol Distearate, Morus Alba Fruit Extract, Cocos Nucifera (Coconut) Fruit Extract, Olea Europaea (Olive) Fruit Extract, Honey Extract (Mel, Extrait de miel), Hydrolyzed Silk, Panthenol, Tocopheryl Acetate, Coco-Glucoside, Sodium Chloride, Glyceryl Oleate, Glyceryl Stearate, Glycerin, Glycereth-26, Lauryl Lactyl Lactate, Triethylene Glycol, Butylene Glycol, Disodium EDTA, Sodium Hydroxide, Propylene Glycol, Benzophenone-4, Benzoic Acid, Benzyl Alcohol, Methylchloroisothiazolinone, Methylisothiazolinone, Mica, Titanium Dioxide (CI 77891), Yellow 5 (CI 19140), Red 33 (CI 17200), Blue 1 (CI 42090).

COMPANY INFORMATION

Bath & Body Works, Distr.
Reynoldsburg, Ohio 43068
1-800-395-1001
www.bathandbodyworks.com